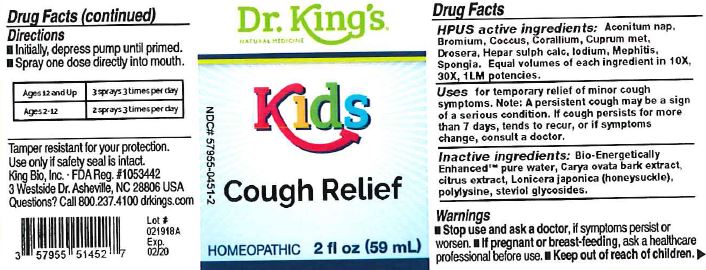 DRUG LABEL: Kids Cough Relief
NDC: 57955-0451 | Form: LIQUID
Manufacturer: King Bio Inc
Category: homeopathic | Type: HUMAN OTC DRUG LABEL
Date: 20180314

ACTIVE INGREDIENTS: ACONITUM NAPELLUS 10 [hp_X]/59 mL; BROMINE 10 [hp_X]/59 mL; PROTORTONIA CACTI 10 [hp_X]/59 mL; CORALLIUM RUBRUM EXOSKELETON 10 [hp_X]/59 mL; COPPER 10 [hp_X]/59 mL; DROSERA ROTUNDIFOLIA 10 [hp_X]/59 mL; CALCIUM SULFIDE 10 [hp_X]/59 mL; IODINE 10 [hp_X]/59 mL; MEPHITIS MEPHITIS ANAL GLAND FLUID 10 [hp_X]/59 mL; SPONGIA OFFICINALIS SKELETON, ROASTED 10 [hp_X]/59 mL
INACTIVE INGREDIENTS: WATER; CARYA OVATA BARK; CITRUS BIOFLAVONOIDS; LONICERA JAPONICA FLOWER; POLYEPSILON-LYSINE (4000 MW); REBAUDIOSIDE A

Kids Cough Relief

HPUS Active Ingredients

Aconitum nap, Bromium, Coccus, Coallium, Cuprum met, Drosera, Hepar sulph calc, Iodium, Mephitis, Spongia.

Equal volumes of each ingredient in 10X, 30C, 1LM potencies.

Uses

for temporary relief of minor cough symptoms. Note: A persistent cough may be a sign of a serios condition. If cough persist for more than 7 days, tends to recur, or if symptoms change, consult a doctor.

Inactive Ingredients

Bio-Energetically Enhanced pure water, Carya ovata bark extract, citrus extract, Lonicera japonica (honeysuckle), polylysine, steviol glycosides.

Warnings

Stop use and ask a doctor, if symptoms persist or worsen.

If pregnant or breast-feeding, ask a healthcare professional before use.

Keep out of reach of children.

Directions

Initially, depress pump until primed

Spray one dose directly into mouth

Ages 12 and Up: 3 sprays 3 times per day

Ages 2-12: 2 sprays 3 times per day

PURPOSE

Uses for temporary relief of minor cough symptoms.

Other Information

Tamper resistant for your protection. Use only if safety seal is intact.